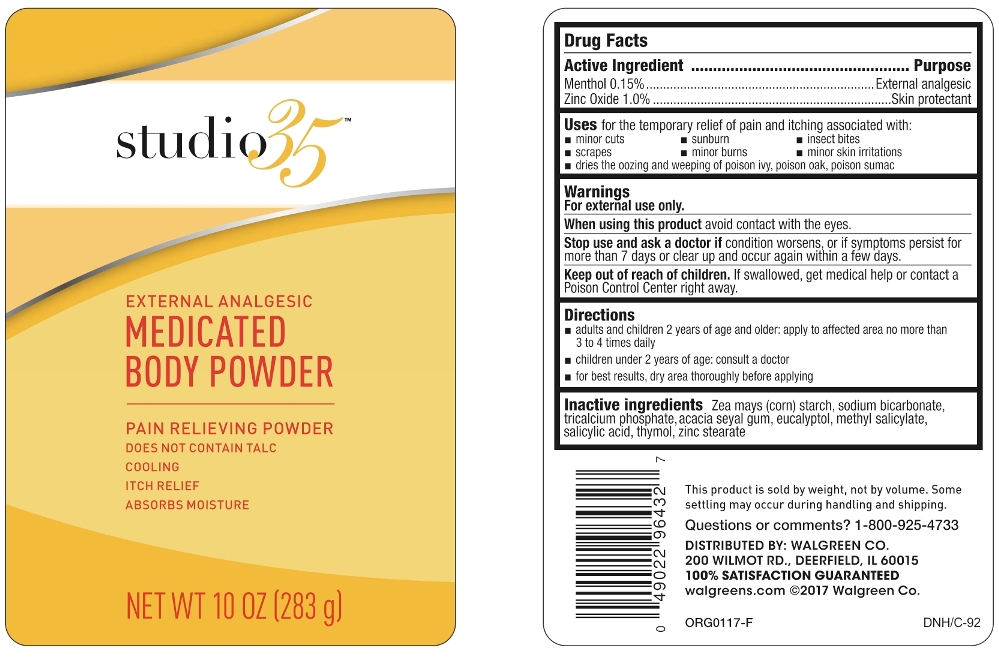 DRUG LABEL: Studio 35 External Analgesic Medicated Body
NDC: 0363-0552 | Form: POWDER
Manufacturer: Walgreen Co
Category: otc | Type: HUMAN OTC DRUG LABEL
Date: 20170208

ACTIVE INGREDIENTS: MENTHOL 1.5 mg/1 g; ZINC OXIDE 10 mg/1 g
INACTIVE INGREDIENTS: STARCH, CORN; SODIUM BICARBONATE; TRICALCIUM PHOSPHATE; GUM TALHA; EUCALYPTOL; METHYL SALICYLATE; SALICYLIC ACID; THYMOL; ZINC STEARATE

Active Ingredients

Menthol 0.15%

Zinc Oxide 1.0%

Purpose

External analgesic

Skin protectant

Uses

for the temporary relief of pain and itching associated with:

- minor cuts
- sunburn
- insect bites
- scrapes
- minor burns
- minor skin irritations
- dries the oozing and weeping of poison ivy, poison oak, poison sumac

Warnings

For external use only.

When using this product

avoid contact with the eyes.

Stop use and ask a doctor

if condition worsens, or if symptoms persist for more than 7 days or clear up and occur again within a few days.

Keep out of reach of children

If swallowed, get medical help or contact a Poison Control Center right away.

Directions

- adults and children 2 years of age and older: apply to affected area no more than 3 to 4 times daily
- children under 2 years of age: consult a doctor
- for best results, dry area thoroughly before applying

Inactive Ingredients

zea mays (corn) starch, sodium bicarbonate, tricalcium phosphate, acacia seyal gum, eucalyptol, methyl salicylate, salicylic acid, thymol, zinc stearate

This product is sold by weight, not by volume. Some settling may occur during handling and shipping.

Questions or comments?

Call 1-800-925-4733

DISTRIBUTED BY: WALGREEN CO.

200 WILMOT RE., DEERFIELD, IL 60015

100% SATISFACTION GUARANTEED

Principal Display Panel

Studio 35

EXTERNAL ANALGESIC

MEDICATED BODY POWDER

PAIN RELIEVING POWDER

DOES NOT CONTAIN TALC

COOLING

ITCH RELEIF

ABSORBS MOISTURE

NET WT 10 OZ (283 g)